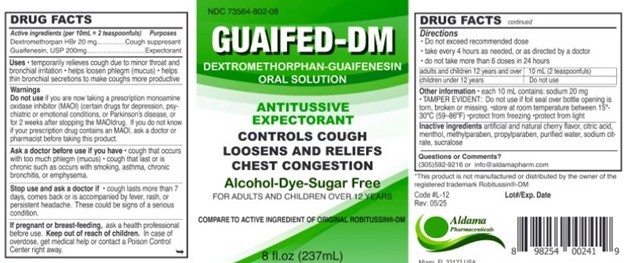 DRUG LABEL: Guaifed DM
NDC: 73564-802 | Form: LIQUID
Manufacturer: Aldama Pharmaceuticals, Inc
Category: otc | Type: HUMAN OTC DRUG LABEL
Date: 20251014

ACTIVE INGREDIENTS: GUAIFENESIN 200 mg/10 mL; DEXTROMETHORPHAN HYDROBROMIDE 20 mg/10 mL
INACTIVE INGREDIENTS: MENTHOL; METHYLPARABEN; PROPYLENE GLYCOL; WATER; SODIUM CITRATE; CITRIC ACID; SUCRALOSE; PROPYLPARABEN

Guaifed DM

Active Ingredients:(per 10ml= 2 teaspoonfuls) Purpose

Guaifenesin 200 mg ................................................................... Expectorant

Dextromethorphan 20mg............................................................ Cough Suppresant

Purpose

Expectorant

Cough Suppresant

Uses:

- Temporarily relieves coiugh due to minor throat and bronchial irritation
- Helps loosen phlegm (mucus)
- helps thin bronchial secretions to make coughs more productive.

Warnings

- Do not use:if you are now takin a prescription monoamine oxidase inhibidor (MAOI) (certain drugs for deression, psychiatric or emotional conditions, or Parkinson's disease, or for two weeks after stoping the MAOI drug. If you do not know if nyour prescription drug contains an MAOI, ask a doctor or pharmacist before taking this product.

Stop use and ask a doctor if

- cough lasts more than 7 days, comes back or is accompanied by fever, rash, or persistent headache. These could be signs of a serious condition.

PREGNANCY OR BREAST FEEDING

If pregnant or breast-feeding,ask a health professional before use.

Keep out of reach of children.

In case of overdose, get medical help or contact a Poison Control Center right away.

Directions

- do not exceed recommended dosage
- take every 4 hours as needed, or as directed by doctor
- do not take more than 6 doses in 24 hours

Age | Dose
adults and children 12 years and over | 10 mL (2 teaspoonfuls)
children under 12 years | Do not use

Other information

- each 10 mL contains:potassium 20 mg
- TAMPER - EVIDENT FEATURE:Do not use if foil seal over bottle opening is torn, broken or missing.
- store between 15° - 30°C (59° - 86°F).
- Protect from freezing
- protect from light

Inactive Ingredients:

Artificial and natural cherry flavor, citric acid, menthol, Methylparaben, Propylene glycol, Propylparaben, purified water, sodium citrate, sucralose

Questions or Comments?305-592-9216 or info@aldamapharm.com

Ask a doctor before use if you have

- cough that occurs with too much phlegm (mucus)
- cough that last or is chronic such as occurs with smoking, asthma, chronic bronchitis, or emphysema